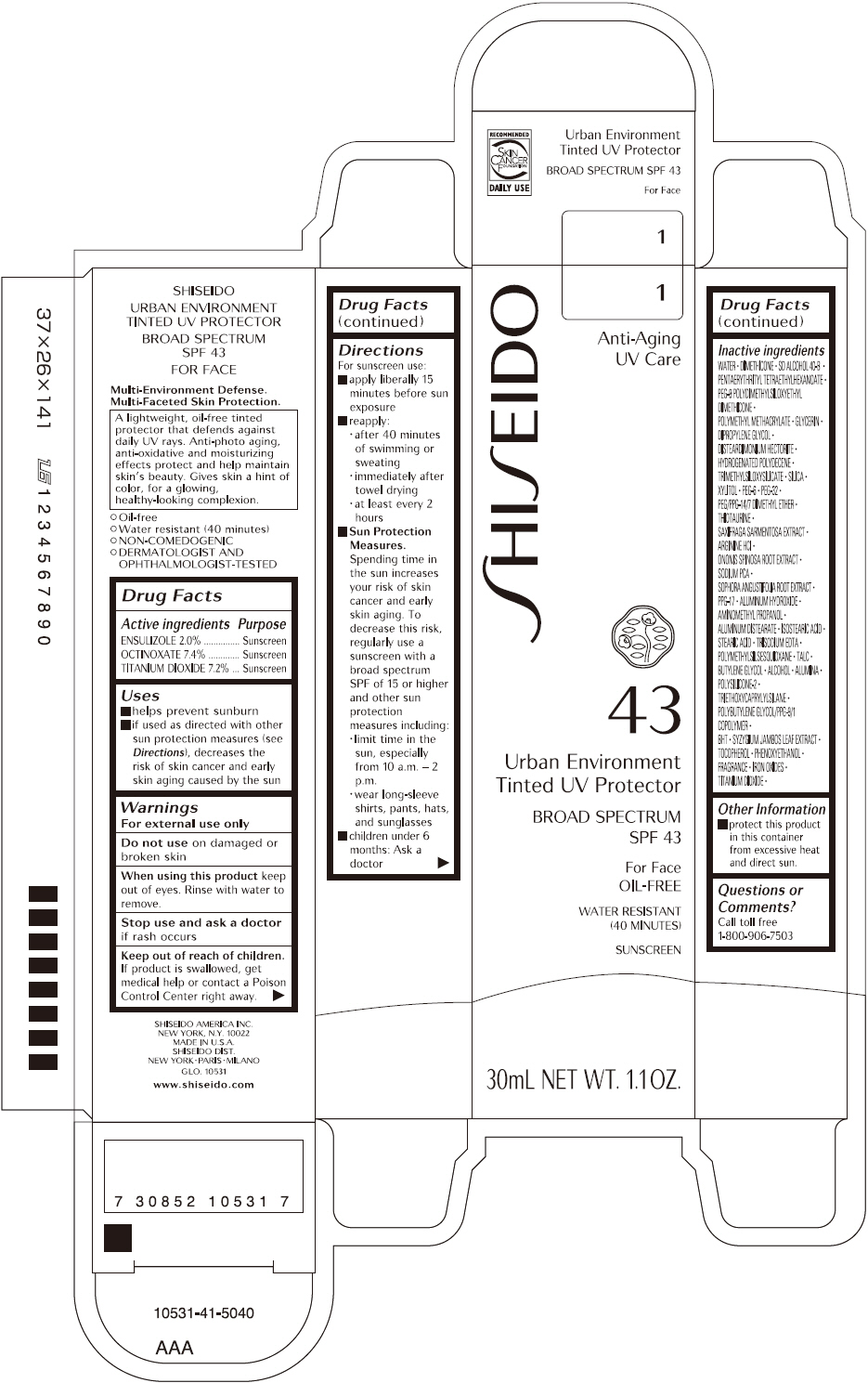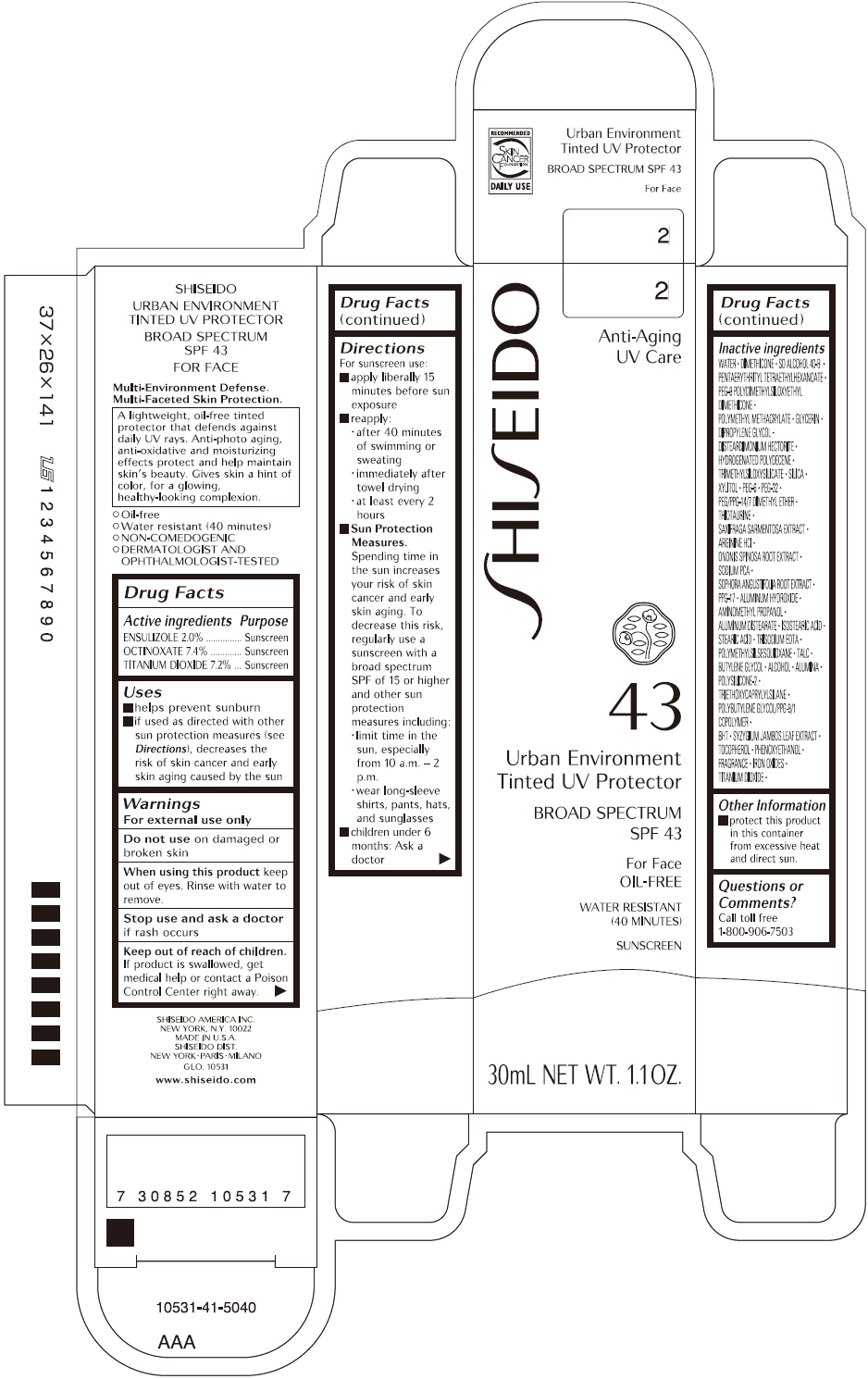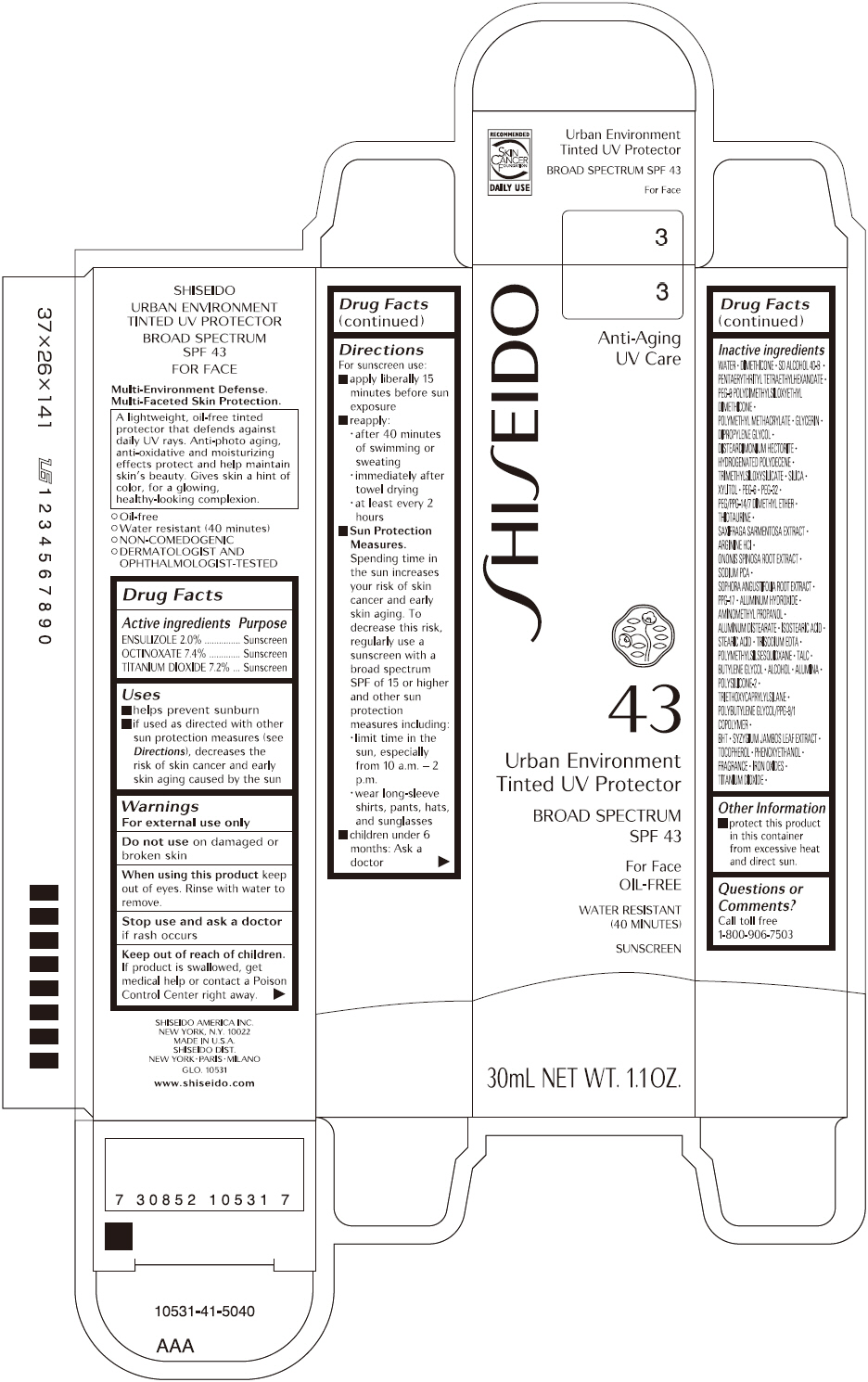 DRUG LABEL: SHISEIDO URBAN ENVIRONMENT TINTED UV PROTECTOR 
NDC: 52686-339 | Form: CREAM
Manufacturer: SHISEIDO AMERICA INC.
Category: otc | Type: HUMAN OTC DRUG LABEL
Date: 20191220

ACTIVE INGREDIENTS: ENSULIZOLE 656 mg/32.79 g; OCTINOXATE 2426 mg/32.79 g; TITANIUM DIOXIDE 2361 mg/32.79 g
INACTIVE INGREDIENTS: WATER; DIMETHICONE; PENTAERYTHRITYL TETRAETHYLHEXANOATE; GLYCERIN; DIPROPYLENE GLYCOL; HYDROGENATED POLYDECENE (550 MW); TRIMETHYLSILOXYSILICATE (M/Q 0.6-0.8); SILICON DIOXIDE; XYLITOL; POLYETHYLENE GLYCOL 300; POLYETHYLENE GLYCOL 1500; PEG/PPG-14/7 DIMETHYL ETHER; THIOTAURINE; SAXIFRAGA STOLONIFERA LEAF; ARGININE HYDROCHLORIDE; ONONIS SPINOSA ROOT; SODIUM PYRROLIDONE CARBOXYLATE; SOPHORA FLAVESCENS ROOT; PPG-17; ALUMINUM HYDROXIDE; AMINOMETHYLPROPANOL; ALUMINUM DISTEARATE; ISOSTEARIC ACID; STEARIC ACID; EDETATE TRISODIUM; POLYMETHYLSILSESQUIOXANE (4.5 MICRONS); TALC; BUTYLENE GLYCOL; ALCOHOL; ALUMINUM OXIDE; TRIETHOXYCAPRYLYLSILANE; BUTYLATED HYDROXYTOLUENE; SYZYGIUM JAMBOS LEAF; .ALPHA.-TOCOPHEROL; PHENOXYETHANOL; FERRIC OXIDE RED; FERRIC OXIDE YELLOW

SHISEIDO URBAN ENVIRONMENT TINTED UV PROTECTOR

Drug Facts

ACTIVE INGREDIENT

ACTIVE INGREDIENTS: | Purpose
ENSULIZOLE 2.0% | Sunscreen
OCTINOXATE 7.4% | Sunscreen
TITANIUM DIOXIDE 7.2% | Sunscreen

Uses

- helps prevent sunburn
- if used as directed with other sun protection measures (see Directions), decreases the risk of skin cancer and early skin aging caused by the sun

Warnings

For external use only

Do not use on damaged or broken skin

When using this product keep out of eyes. Rinse with water to remove.

Stop use and ask a doctor if rash occurs

Keep out of reach of children. If product is swallowed, get medical help or contact a Poison Control Center right away.

Directions

For sunscreen use:

- apply liberally 15 minutes before sun exposure
- reapply:
  - after 40 minutes of swimming or sweating
  - immediately after towel drying
  - at least every 2 hours
- Sun Protection Measures. Spending time in the sun increases your risk of skin cancer and early skin aging. To decrease this risk, regularly use a sunscreen with a broad spectrum SPF of 15 or higher and other sun protection measures including:
  - limit time in the sun, especially from 10 a.m. – 2 p.m.
  - wear long-sleeve shirts, pants, hats, and sunglasses
- children under 6 months: Ask a doctor

Inactive Ingredients

WATER, DIMETHICONE, SD ALCOHOL 40-B, PENTAERYTHRITYL TETRAETHYLHEXANOATE, PEG-9 POLYDIMETHYLSILOXYETHYL DIMETHICONE, POLYMETHYL METHACRYLATE, GLYCERIN, DIPROPYLENE GLYCOL, DISTEARDIMONIUM HECTORITE, HYDROGENATED POLYDECENE, TRIMETHYLSILOXYSILICATE, SILICA, XYLITOL, PEG-6, PEG-32, PEG/PPG-14/7 DIMETHYL ETHER, THIOTAURINE, SAXIFRAGA SARMENTOSA EXTRACT, ARGININE HCl, ONONIS SPINOSA ROOT EXTRACT, SODIUM PCA, SOPHORA ANGUSTIFOLIA ROOT EXTRACT, PPG-17, ALUMINUM HYDROXIDE, AMINOMETHYL PROPANOL, ALUMINUM DISTEARATE, ISOSTEARIC ACID, STEARIC ACID, TRISODIUM EDTA, POLYMETHYLSILSESQUIOXANE, TALC, BUTYLENE GLYCOL, ALCOHOL, ALUMINA, POLYSILICONE-2, TRIETHOXYCAPRYLYLSILANE, POLYBUTYLENE GLYCOL/PPG-9/1 COPOLYMER, BHT, SYZYGIUM JAMBOS LEAF EXTRACT, TOCOPHEROL, PHENOXYETHANOL, FRAGRANCE, IRON OXIDES, TITANIUM DIOXIDE,

Other information

- protect this product in this container from excessive heat and direct sun.

Questions or comments?

Call toll free 1-800-906-7503

SHISEIDO AMERICA INC.
NEW YORK, N.Y. 10022

SHISEIDO DIST.
NEW YORK • PARIS • MILANO

PRINCIPAL DISPLAY PANEL - 30mL Tube Carton

SHISEIDO

1

Anti-Aging
UV Care

43

Urban Environment
Tinted UV Protector

BROAD SPECTRUM
SPF 43

For Face
OIL-FREE

WATER RESISTANT
(40 MINUTES)

SUNSCREEN

30mL NET WT. 1.1OZ.

PRINCIPAL DISPLAY PANEL - 30mL Tube Carton

SHISEIDO

2

Anti-Aging
UV Care

43

Urban Environment
Tinted UV Protector

BROAD SPECTRUM
SPF 43

For Face
OIL-FREE

WATER RESISTANT
(40 MINUTES)

SUNSCREEN

30mL NET WT. 1.1OZ.

PRINCIPAL DISPLAY PANEL - 30mL Tube Carton

SHISEIDO

3

Anti-Aging
UV Care

43

Urban Environment
Tinted UV Protector

BROAD SPECTRUM
SPF 43

For Face
OIL-FREE

WATER RESISTANT
(40 MINUTES)

SUNSCREEN

30mL NET WT. 1.1OZ.